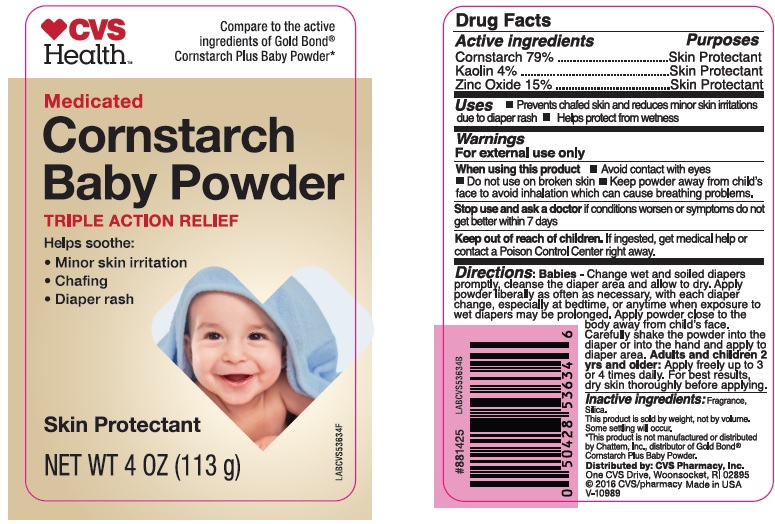 DRUG LABEL: Medicated Cornstarch Baby Powder
NDC: 42669-231 | Form: POWDER
Manufacturer: Davion, Inc.
Category: otc | Type: HUMAN OTC DRUG LABEL
Date: 20251229

ACTIVE INGREDIENTS: STARCH, CORN 89.27 g/113 g; ZINC OXIDE 16.95 g/113 g; KAOLIN 4.52 g/113 g
INACTIVE INGREDIENTS: SILICON DIOXIDE

Medicated Cornstarch Baby Powder

Active Ingredients

Corn Starch 79%

Kaolin 4%

Zinc Oxide 15%

Purposes

Skin Protectant

Uses

- Prevents chafed skin and reduces minor skin irritations due to diaper rash
- Helps protect from wetness

Warnings

For external use only.

When using this product

- Avoid contact with eyes
- Do not use on broken skin
- Keep powder away from child's face to avoid inhalation which can cause breathing problems

Stop use and ask a doctor if

- If conditions worsen or symptoms do not get better within 7 days

Keep out of reach of children.

If ingested, get medical help or contact a Poison Control Center immediately.

Directions

Babies: Change wet and soiled diaper promptly, cleanse the diaper area and allow to dry. Apply powder liberally as often as necessary, with each diaper change, especially at bedtime, or anytime when exposure to wet diapers may be prolonged. Apply powder close to the body away from child's face. Carefully shake the powder into the diaper or into the hand and apply to diaper area.

Adults and children 2 years and older: apply freely up to 3 or 4 times daily. For best results, dry skin thoroughly before applying.

Inactive ingredients

Fragrance, Silica